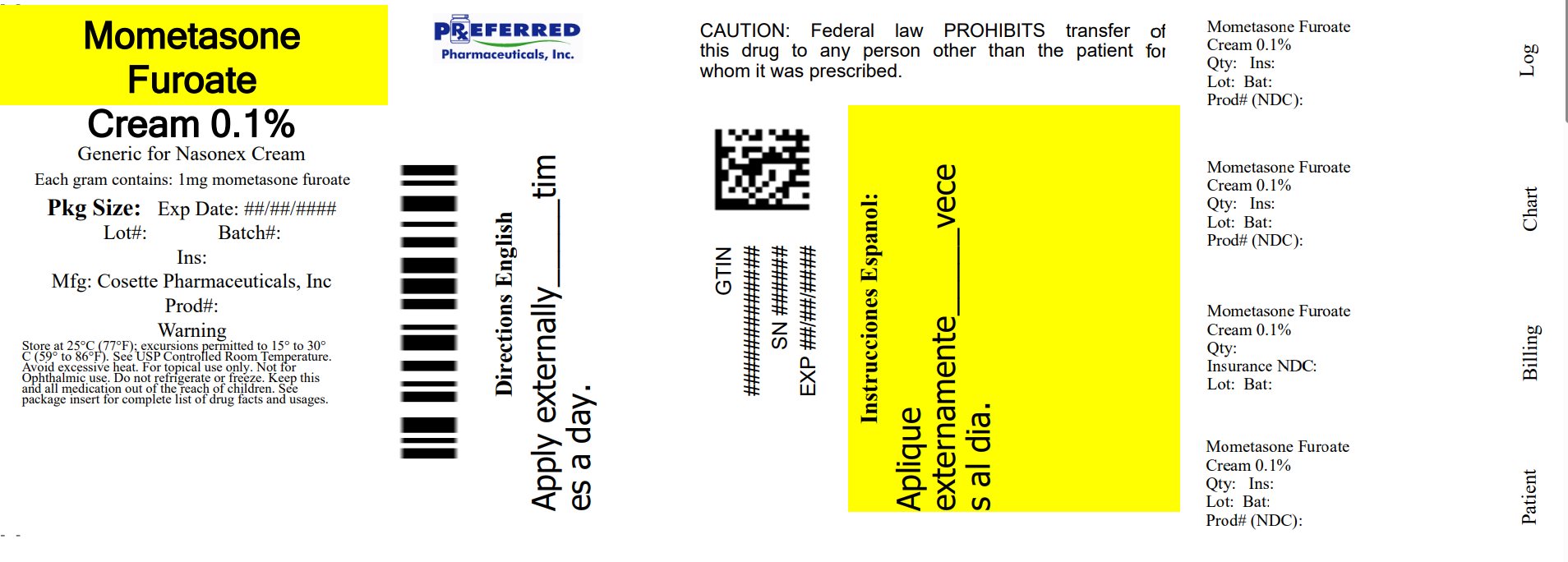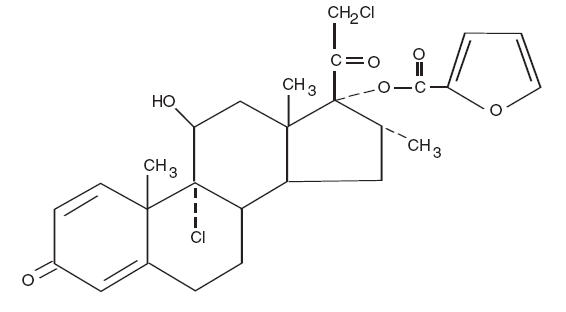 DRUG LABEL: Mometasone Furoate
NDC: 68788-4075 | Form: CREAM
Manufacturer: Preferred Pharmaceuticals Inc.
Category: prescription | Type: HUMAN PRESCRIPTION DRUG LABEL
Date: 20260127

ACTIVE INGREDIENTS: MOMETASONE FUROATE 1 mg/1 g
INACTIVE INGREDIENTS: HEXYLENE GLYCOL; PHOSPHORIC ACID; PROPYLENE GLYCOL MONOSTEARATE; STEARYL ALCOHOL; TITANIUM DIOXIDE; WHITE WAX; PETROLATUM; WATER; POLYOXYL 20 CETOSTEARYL ETHER; ALUMINUM STARCH OCTENYLSUCCINATE

HIGHLIGHTS OF PRESCRIBING INFORMATION

These highlights do not include all the information needed to use MOMETASONE FUROATE CREAM, USP safely and effectively. See full prescribing information for MOMETASONE FUROATE CREAM, USP.
MOMETASONE FUROATE cream, USP for topical use
Initial U.S. Approval: 1987

RECENT MAJOR CHANGES

Warnings and Precautions
Ophthalmic Adverse Reactions (5.2) 05/2018

1 INDICATIONS AND USAGE

Mometasone furoate cream, USP, 0.1% is a corticosteroid indicated for the relief of the inflammatory and pruritic manifestations of corticosteroid-responsive dermatoses in patients ≥ 2 years of age. (1)

2 DOSAGE AND ADMINISTRATION

• Apply a thin film to the affected skin areas once daily. (2)
• Discontinue therapy when control is achieved. (2)
• If no improvement is seen within 2 weeks, reassess diagnosis. (2)
• Do not use with occlusive dressings unless directed by a physician. (2)

3 DOSAGE FORMS AND STRENGTHS

• Cream, 0.1%. (3)

4 CONTRAINDICATIONS

Mometasone furoate cream, USP, 0.1% is contraindicated in those patients with a history of hypersensitivity to any of the components in the preparation. (4)

5 WARNINGS AND PRECAUTIONS

• Reversible HPA axis suppression with the potential for glucocorticosteroid insufficiency after withdrawal of treatment, Cushing's syndrome, and hyperglycemia may occur due to systemic absorption. Patients applying a topical steroid to a large surface area or to areas under occlusion should be evaluated periodically for evidence of HPA axis suppression. Modify use should HPA axis suppression develop. (5.1, 8.4)
• Pediatric patients may be more susceptible to systemic toxicity. (5.1, 8.4)
• May increase the risk of cataracts and glaucoma. If visual symptoms occur, consider referral to an ophthalmologist. (5.2)

6 ADVERSE REACTIONS

Most common adverse reactions are: burning, pruritus, and skin atrophy. (6) To report SUSPECTED ADVERSE REACTIONS, contact Cosette Pharmaceuticals, Inc. at 1-800-922-1038 or FDA at 1-800-FDA-1088 or www.fda.gov/medwatch.

FULL PRESCRIBING INFORMATION

1 INDICATIONS AND USAGE

Mometasone furoate cream, USP, 0.1% is a corticosteroid indicated for the relief of the inflammatory and pruritic manifestations of corticosteroid-responsive dermatoses in patients 2 years of age or older.

2 DOSAGE AND ADMINISTRATION

Apply a thin film of mometasone furoate cream, USP, 0.1% to the affected skin areas once daily. Mometasone furoate cream, USP, 0.1% may be used in pediatric patients 2 years of age or older. Since safety and efficacy of mometasone furoate cream, USP, 0.1% have not been established in pediatric patients below 2 years of age; use in this age group is not recommended [see Warnings and Precautions (5.1) and Use in Specific Populations (8.4)] .
Therapy should be discontinued when control is achieved. If no improvement is seen within 2 weeks, reassessment of diagnosis may be necessary. [see Warnings and Precautions (5.1)] .
Do not use mometasone furoate cream, USP, 0.1% with occlusive dressings unless directed by a physician. Do not apply mometasone furoate cream, USP, 0.1% in the diaper area if the patient still requires diapers or plastic pants, as these garments may constitute occlusive dressing.
Avoid contact with eyes. Wash hands after each application. Avoid use on the face, groin, or axillae.
Mometasone furoate cream, USP, 0.1% is for topical use only. It is not for oral, ophthalmic, or intravaginal use.

3 DOSAGE FORMS AND STRENGTHS

Cream, 0.1%. Each gram of mometasone furoate cream, USP, 0.1% contains 1 mg of mometasone furoate in a white to off-white smooth and homogenous cream base.

4 CONTRAINDICATIONS

Mometasone furoate cream, USP, 0.1% is contraindicated in those patients with a history of hypersensitivity to any of the components in the preparation.

5 WARNINGS AND PRECAUTIONS

5.1 Effects on Endocrine System

Systemic absorption of topical corticosteroids can produce reversible hypothalamic-pituitary-adrenal (HPA) axis suppression with the potential for glucocorticosteroid insufficiency. This may occur during treatment or after withdrawal of treatment. Manifestations of Cushing's syndrome, hyperglycemia, and glucosuria can also be produced in some patients by systemic absorption of topical corticosteroids while on treatment. Factors that predispose a patient using a topical corticosteroid to HPA axis suppression include the use of high-potency steroids, large treatment surface areas, prolonged use, use of occlusive dressings, altered skin barrier, liver failure and young age.
Because of the potential for systemic absorption, use of topical corticosteroids may require that patients be periodically evaluated for HPA axis suppression. This may be done by using the adrenocorticotropic hormone (ACTH) stimulation test.
In a study evaluating the effects of mometasone furoate cream, USP, on the HPA axis, 15 grams were applied twice daily for 7 days to six adult subjects with psoriasis or atopic dermatitis. The results show that the drug caused a slight lowering of adrenal corticosteroid secretion.
If HPA axis suppression is noted, an attempt should be made to gradually withdraw the drug, to reduce the frequency of application, or to substitute a less potent corticosteroid. Recovery of HPA axis function is generally prompt upon discontinuation of topical corticosteroids. Infrequently, signs and symptoms of glucocorticosteroid insufficiency may occur, requiring supplemental systemic corticosteroids.
Pediatric patients may be more susceptible to systemic toxicity from equivalent doses due to their larger skin surface to body mass ratios [ seeUse in Specific Populations (8.4) ].

5.2 Ophthalmic Adverse Reactions

Use of topical corticosteroids may increase the risk of posterior subcapsular cataracts and glaucoma. Cataracts and glaucoma have been reported in postmarketing experience with the use of topical corticosteroids, including the topical mometasone products [see Adverse Reactions (6.2)] .

Avoid contact of mometasone furoate cream, USP, 0.1% with eyes. Advise patients to report any visual symptoms and consider referral to an ophthalmologist for evaluation.

5.3 Allergic Contact Dermatitis

If irritation develops, mometasone furoate cream, USP, 0.1% should be discontinued and appropriate therapy instituted. Allergic contact dermatitis with corticosteroids is usually diagnosed by observing a failure to heal rather than noting a clinical exacerbation as with most topical products not containing corticosteroids. Such an observation should be corroborated with appropriate diagnostic patch testing.

5.4 Concomitant Skin Infections

If concomitant skin infections are present or develop, an appropriate antifungal or antibacterial agent should be used. If a favorable response does not occur promptly, use of mometasone furoate cream, USP, 0.1% should be discontinued until the infection has been adequately controlled.

6 ADVERSE REACTIONS

6.1 Clinical Trials Experience

Because clinical trials are conducted under widely varying conditions, adverse reaction rates observed in the clinical trials of a drug cannot be directly compared to rates in the clinical trials of another drug and may not reflect the rates observed in clinical practice.

In controlled clinical trials involving 319 subjects, the incidence of adverse reactions associated with the use of mometasone furoate cream, USP, 0.1% was 1.6%. Reported reactions included burning, pruritus, and skin atrophy. Reports of rosacea associated with the use of mometasone furoate cream, USP, 0.1% have also been received. In controlled clinical trials (n=74) involving pediatric subjects 2 to 12 years of age, the incidence of adverse experiences associated with the use of mometasone furoate cream, USP, 0.1% was approximately 7%. Reported reactions included stinging, pruritus, and furunculosis.

The following adverse reactions were reported to be possibly or probably related to treatment with mometasone furoate cream, USP, 0.1% during clinical trials in 4% of 182 pediatric subjects 6 months to 2 years of age: decreased glucocorticoid levels, 2; paresthesia, 2; folliculitis, 1; moniliasis, 1; bacterial infection; 1 skin depigmentation, 1. The following signs of skin atrophy were also observed among 97 subjects treated with mometasone furoate cream, USP, 0.1% in a clinical trial: shininess, 4; telangiectasia, 1; loss of elasticity, 4; loss of normal skin markings, 4; thinness, 1; and bruising, 1.

6.2 Postmarketing Experience

Because adverse reactions are reported voluntarily from a population of uncertain size, it is not always possible to reliably estimate their frequency or establish a causal relationship to drug exposure.

Postmarketing reports for local adverse reactions to topical corticosteroids include irritation, dryness, folliculitis, hypertrichosis, acneiform eruptions, hypopigmentation, perioral dermatitis, allergic contact dermatitis, secondary infection, striae, and miliaria. These adverse reactions may occur more frequently with the use of occlusive dressings.

Postmarketing reports for ophthalmic adverse reactions to topical corticosteroids include blurred vision, cataracts, glaucoma, increased intraocular pressure, and central serous chorioretinopathy.

To report SUSPECTED ADVERSE REACTIONS, contact Cosette Pharmaceuticals, Inc. at 1-800-922-1038 or FDA at 1-800-FDA-1088 or www.fda.gov/medwatch.

7 DRUG INTERACTIONS

No drug-drug interaction studies have been conducted with mometasone furoate cream, USP, 0.1%.

8 USE IN SPECIFIC POPULATIONS

8.1 Pregnancy

Teratogenic Effects Pregnancy Category C:
There are no adequate and well-controlled studies in pregnant women. Therefore, mometasone furoate cream, USP, 0.1% should be used during pregnancy only if the potential benefit justifies the potential risk to the fetus.
Corticosteroids have been shown to be teratogenic in laboratory animals when administered systemically at relatively low dosage levels. Some corticosteroids have been shown to be teratogenic after dermal application in laboratory animals.
When administered to pregnant rats, rabbits, and mice, mometasone furoate increased fetal malformations. The doses that produced malformations also decreased fetal growth, as measured by lower fetal weights and/or delayed ossification. Mometasone furoate also caused dystocia and related complications when administered to rats during the end of pregnancy.
In mice, mometasone furoate caused cleft palate at subcutaneous doses of 60 mcg/kg and above. Fetal survival was reduced at 180 mcg/kg. No toxicity was observed at 20 mcg/kg. (Doses of 20, 60, and 180 mcg/kg in the mouse are approximately 0.01, 0.02, and 0.05 times the estimated maximum clinical topical dose from mometasone furoate cream, USP, 0.1% on a mcg/m ^2basis.)
In rats, mometasone furoate produced umbilical hernias at topical doses of 600 mcg/kg and above. A dose of 300 mcg/kg produced delays in ossification, but no malformations. (Doses of 300 and 600 mcg/kg in the rat are approximately 0.2 and 0.4 times the estimated maximum clinical topical dose from mometasone furoate cream, USP, 0.1% on a mcg/m ^2basis.)
In rabbits, mometasone furoate caused multiple malformations (e.g., flexed front paws, gallbladder agenesis, umbilical hernia, hydrocephaly) at topical doses of 150 mcg/kg and above (approximately 0.2 times the estimated maximum clinical topical dose from mometasone furoate cream, USP, 0.1% on a mcg/m ^2basis). In an oral study, mometasone furoate increased resorptions and caused cleft palate and/or head malformations (hydrocephaly and domed head) at 700 mcg/kg. At 2800 mcg/kg most litters were aborted or resorbed. No toxicity was observed at 140 mcg/kg. (Doses at 140, 700, and 2800 mcg/kg in the rabbit are approximately 0.2, 0.9, and 3.6 times the estimated maximum clinical topical dose from mometasone furoate cream, USP, 0.1% on a mcg/m ^2basis.)
When rats received subcutaneous doses of mometasone furoate throughout pregnancy or during the later stages of pregnancy, 15 mcg/kg caused prolonged and difficult labor and reduced the number of live births, birth weight, and early pup survival. Similar effects were not observed at 7.5 mcg/kg. (Doses of 7.5 and 15 mcg/kg in the rat are approximately 0.005 and 0.01 times the estimated maximum clinical topical dose from mometasone furoate cream, USP, 0.1% on a mcg/m ^2basis.)

8.3 Nursing Mothers

Systemically administered corticosteroids appear in human milk and could suppress growth, interfere with endogenous corticosteroid production, or cause other untoward effects. It is not known whether topical administration of corticosteroids could result in sufficient systemic absorption to produce detectable quantities in human milk. Because many drugs are excreted in human milk, caution should be exercised when mometasone furoate cream, USP,0.1% is administered to a nursing woman.

8.4 Pediatric Use

Mometasone furoate cream, USP, 0.1% may be used with caution in pediatric patients 2 years of age or older, although the safety and efficacy of drug use for longer than 3 weeks have not been established. Since safety and efficacy of mometasone furoate cream, USP, 0.1% have not been established in pediatric patients below 2 years of age, its use in this age group is not recommended.
In a pediatric trial, 24 atopic dermatitis subjects, of whom 19 subjects were age 2 to 12 years, were treated with mometasone furoate cream, USP, 0.1% once daily. The majority of subjects cleared within 3 weeks. Mometasone furoate cream, USP, 0.1% caused HPA axis suppression in approximately 16% of pediatric subjects ages 6 to 23 months, who showed normal adrenal function by Cortrosyn test before starting treatment, and were treated for approximately 3 weeks over a mean body surface area of 41% (range 15%-94%). The criteria for suppression were: basal cortisol level of ≤5 mcg/dL, 30-minute post-stimulation level of ≤18 mcg/dL, or an increase of <7 mcg/dL. Follow-up testing 2 to 4 weeks after trial completion, available for 5 of the subjects, demonstrated suppressed HPA axis function in 1 subject, using these same criteria. Long-term use of topical corticosteroids has not been studied in this population [ see Clinical Pharmacology (12.2) ].
Because of a higher ratio of skin surface area to body mass, pediatric patients are at a greater risk than adults of HPA axis suppression and Cushing's syndrome when they are treated with topical corticosteroids. They are, therefore, also at greater risk of adrenal insufficiency during and/or after withdrawal of treatment. Pediatric patients may be more susceptible than adults to skin atrophy, including striae, when they are treated with topical corticosteroids. Pediatric patients applying topical corticosteroids to greater than 20% of body surface are at higher risk of HPA axis suppression.
HPA axis suppression, Cushing's syndrome, linear growth retardation, delayed weight gain, and intracranial hypertension have been reported in pediatric patients receiving topical corticosteroids. Manifestations of adrenal suppression in children include low plasma cortisol levels and an absence of response to ACTH stimulation. Manifestations of intracranial hypertension include bulging fontanelles, headaches, and bilateral papilledema.
Mometasone furoate cream, USP, 0.1% should not be used in the treatment of diaper dermatitis.

8.5 Geriatric Use

Clinical studies of mometasone furoate cream, USP, 0.1% included 190 subjects who were 65 years of age and over and 39 subjects who were 75 years of age and over. No overall differences in safety or effectiveness were observed between these subjects and younger subjects, and other reported clinical experience has not identified differences in responses between the elderly and younger patients. However, greater sensitivity of some older individuals cannot be ruled out.

10 OVERDOSAGE

Topically applied mometasone furoate cream, USP, 0.1% can be absorbed in sufficient amounts to produce systemic effects [ see Warnings and Precautions (5.1) ].

11 DESCRIPTION

Mometasone furoate cream, USP, 0.1% contains mometasone furoate for topical use. Mometasone furoate is a synthetic corticosteroid with anti-inflammatory activity.
Chemically, mometasone furoate is 9α,21-dichloro-11β,17-dihydroxy-16α-methylpregna-1,4-diene-3,20-dione 17-(2- furoate), with the empirical formula C 27H 30Cl 2O 6, a molecular weight of 521.4 and the following structural formula:

Mometasone furoate is a white to off-white powder practically insoluble in water, slightly soluble in octanol, and moderately soluble in ethyl alcohol.
Each gram of mometasone furoate cream, USP, 0.1% contains 1 mg mometasone furoate, USP in a cream base of hexylene glycol, phosphoric acid, propylene glycol stearate, stearyl alcohol and ceteareth-20, titanium dioxide, aluminum starch octenylsuccinate, white wax, white petrolatum, and purified water.

12 CLINICAL PHARMACOLOGY

12.1 Mechanism of Action

Like other topical corticosteroids, mometasone furoate has anti-inflammatory, antipruritic, and vasoconstrictive properties. The mechanism of the anti-inflammatory activity of the topical steroids, in general, is unclear. However, corticosteroids are thought to act by the induction of phospholipase A 2inhibitory proteins, collectively called lipocortins. It is postulated that these proteins control the biosynthesis of potent mediators of inflammation such as prostaglandins and leukotrienes by inhibiting the release of their common precursor arachidonic acid. Arachidonic acid is released from membrane phospholipids by phospholipase A 2.

12.2 Pharmacodynamics

Studies performed with mometasone furoate cream, USP, 0.1% indicate that it is in the medium range of potency as compared with other topical corticosteroids.
In a study evaluating the effects of mometasone furoate cream, USP, on the HPA axis, 15 grams were applied twice daily for 7 days to six adult subjects with psoriasis or atopic dermatitis. The cream was applied without occlusion to at least 30% of the body surface. The results showed that the drug caused a slight lowering of adrenal corticosteroid secretion [ see Warnings and Precautions (5.1) ].
Ninety-seven pediatric subjects ages 6 to 23 months with atopic dermatitis, were enrolled in an open-label, HPA axis safety study. Mometasone furoate cream, USP, 0.1% was applied once daily for approximately 3 weeks over a mean body surface area of 41% (range 15%-94%). In approximately 16% of subjects who showed normal adrenal function by Cortrosyn test before starting treatment, adrenal suppression was observed at the end of treatment with mometasone furoate cream, USP, 0.1%. The criteria for suppression were: basal cortisol level of ≤5 mcg/dL, 30-minute post-stimulation level of ≤18 mcg/dL, or an increase of <7 mcg/dL. Follow-up testing 2 to 4 weeks after stopping treatment, available for 5 of the subjects, demonstrated suppressed HPA axis function in one subject, using these same criteria [ seeUse in Specific Populations(8.4) ].

12.3 Pharmacokinetics

The extent of percutaneous absorption of topical corticosteroids is determined by many factors including the vehicle and the integrity of the epidermal barrier. Studies in humans indicate that approximately 0.4% of the applied dose of mometasone furoate cream, USP, 0.1% enters the circulation after 8 hours of contact on normal skin without occlusion. Inflammation and/or other disease processes in the skin may increase percutaneous absorption.

13 NONCLINICAL TOXICOLOGY

13.1 Carcinogenesis, Mutagenesis, Impairment of Fertility

Long-term animal studies have not been performed to evaluate the carcinogenic potential of mometasone furoate cream, USP, 0.1%. Long-term carcinogenicity studies of mometasone furoate were conducted by the inhalation route in rats and mice. In a 2-year carcinogenicity study in Sprague Dawley rats, mometasone furoate demonstrated no statistically significant increase of tumors at inhalation doses up to 67 mcg/kg (approximately 0.04 times the estimated maximum clinical topical dose from mometasone furoate cream, USP, 0.1% on a mcg/m ^2basis). In a 19-month carcinogenicity study in Swiss CD-1 mice, mometasone furoate demonstrated no statistically significant increase in the incidence of tumors at inhalation doses up to 160 mcg/kg (approximately 0.05 times the estimated maximum clinical topical dose from mometasone furoate cream, USP, 0.1% on a mcg/m ^2basis).
Mometasone furoate increased chromosomal aberrations in an in vitroChinese hamster ovary cell assay, but did not increase chromosomal aberrations in an in vitroChinese hamster lung cell assay. Mometasone furoate was not mutagenic in the Ames test or mouse lymphoma assay, and was not clastogenic in an in vivomouse micronucleus assay, a rat bone marrow chromosomal aberration assay, or a mouse male germ-cell chromosomal aberration assay. Mometasone furoate also did not induce unscheduled DNA synthesis in vivoin rat hepatocytes.
In reproductive studies in rats, impairment of fertility was not produced in male or female rats by subcutaneous doses up to 15 mcg/kg (approximately 0.01 times the estimated maximum clinical topical dose from mometasone furoate cream 0.1% on a mcg/m ^2basis).

14 CLINICAL STUDIES

The safety and efficacy of the mometasone furoate cream, USP, 0.1% for the treatment of corticosteroid-responsive dermatoses were evaluated in two randomized, double-blind, vehicle-controlled clinical trials, one in psoriasis and one in atopic dermatitis. A total 366 subjects (12-81 years of age), of whom 177 received mometasone furoate cream, USP, 0.1% and 181 subjects received vehicle cream, were evaluated in these trials. Mometasone furoate cream, USP, 0.1% or the vehicle cream were applied once daily for 21 days.
The two trials showed mometasone furoate cream, USP, 0.1% is effective in the treatment of psoriasis and atopic dermatitis.

16 HOW SUPPLIED/STORAGE AND HANDLING

Mometasone furoate cream, USP, 0.1% is supplied in 45 g (NDC 68788-4075-4) tubes; boxes of one.
Store at 25°C (77°F); excursions permitted to 15-30°C (59-86°F) [see USP Controlled Room Temperature]. Avoid excessive heat.

17 PATIENT COUNSELING INFORMATION

Advise the patient to read the FDA-approved patient labeling (Patient Information).

Inform patients of the following:
• Use mometasone furoate cream, USP, 0.1% as directed by the physician. It is for external use only.
• Avoid contact with the eyes.
• Advise patients to report any visual symptoms to their healthcare providers.
• Do not use mometasone furoate cream, USP, 0.1% on the face, underarms, or groin areas unless directed by the physician.
• Do not use mometasone furoate cream, USP, 0.1% for any disorder other than that for which it was prescribed.
• Do not bandage or otherwise cover or wrap the treated skin area so as to be occlusive, unless directed by the physician.
• Report any signs of local adverse reactions to the physician.
• Advise patients not to use mometasone furoate cream, USP, 0.1% in the treatment of diaper dermatitis. Do not apply mometasone furoate cream, USP, 0.1% in the diaper area, as diapers or plastic pants may constitute occlusive dressing.
• Discontinue therapy when control is achieved. If no improvement is seen within 2 weeks, contact the physician.
• Do not use other corticosteroid-containing products with mometasone furoate cream, USP, 0.1% without first consulting with the physician.

Distributed by:
Cosette Pharmaceuticals, Inc.
South Plainfield, NJ 07080

8-0634CPLNC2 Revised: 03/2022 VC7619

Relabeled By: Preferred Pharmaceuticals Inc.

Patient Information

Mometasone Furoate Cream, USP, 0.1%
(Mo-meta-sone fur-o-ate)

Important information: Mometasone Furoate Cream, USP, 0.1% is for use on skin only.Do not use mometasone furoate cream, USP, 0.1% in your eyes, mouth, or vagina.

What is mometasone furoate cream, USP, 0.1%?

• Mometasone furoate cream, USP, 0.1% is a prescription medicine used on the skin (topical) for the relief of redness, swelling, heat, pain (inflammation) and itching, caused by certain skin problems in people 2 years of age and older.
• It is not known if mometasone furoate cream, USP, 0.1% is safe and effective for use in children under 2 years of age.
• Mometasone furoate cream, USP, 0.1% should not be used in children under 2 years of age.
• It is not known if mometasone furoate cream, USP, 0.1% is safe and effective for use in children longer than 3 weeks.

Do not use mometasone furoate cream, USP, 0.1% if youare allergic to mometasone furoate or any of the ingredients in mometasone furoate cream, USP, 0.1%. See the end of this leaflet for a complete list of ingredients in mometasone furoate cream, USP, 0.1%.

Before using mometasone furoate cream, USP, 0.1%, tell your healthcare provider about all your medical conditions, including if you:

• have a skin infection at the site to be treated. You may also need medicine to treat the skin infection.
• are pregnant or plan to become pregnant. It is not known if mometasone furoate cream, USP, 0.1% will harm your unborn baby.
• are breastfeeding or plan to breastfeed. It is not known if mometasone furoate cream, USP, 0.1% passes into your breast milk. Tell your healthcare provider aboutall the medicines you take,including prescription and over-the-counter medicines, vitamins, and herbal supplements.
Especially tell your healthcare provider if you take other corticosteroid medicines by mouth or use other products on your skin or scalp that contain corticosteroids.

How should I use mometasone furoate cream, USP, 0.1%?• Use mometasone furoate cream, USP, 0.1% exactly as your healthcare provider tells you to use it.
• Apply a thin film of mometasone furoate cream, USP, 0.1% to the affected skin area 1 time each day.
• Tell your healthcare provider if the treated skin area does not get better after 2 weeks of treatment.
• Do not bandage, cover, or wrap the treated skin area unless your healthcare provider tells you to.
• Mometasone furoate cream, USP, 0.1% should not be used to treat diaper rash or redness. Do not apply mometasone furoate cream, USP, 0.1% in the diaper area if wearing diapers or plastic pants.
• Avoid using mometasone furoate cream, USP, 0.1% on the face, groin, or underarms (armpits).
• Wash your hands after applying mometasone furoate cream, USP, 0.1%.

What are the possible side effects of mometasone furoate cream, USP, 0.1%? Mometasone furoate cream, USP, 0.1% may cause serious side effects, including:

• Mometasone furoate cream, USP, 0.1% can pass through your skin.
Too much mometasone furoate cream, USP, 0.1% passing through your skin can cause your adrenal glands to stop working properly. Your healthcare provider may do blood tests to check for adrenal gland problems.
• Vision problems.Topical corticosteroids may increase your chance of developing vision problems such as cataract and glaucoma. Tell your healthcare provider if you develop blurred vision or other vision problems during treatment with mometasone furoate cream, USP, 0.1%.
• Skin problems.Skin problems may happen during treatment with mometasone furoate cream, USP, 0.1%, including allergic reactions (contact dermatitis) and skin infections at the treatment site. Stop using mometasone furoate cream, USP, 0.1% and tell your healthcare provider if you develop any skin reactions such as pain, tenderness, swelling, or problems healing during treatment with mometasone furoate cream, USP, 0.1%.
The most common side effects of mometasone furoate cream, USP, 0.1% includeburning, itching, and thinning of the skin (atrophy). These are not all the possible side effects of mometasone furoate cream, USP, 0.1%. Call your doctor for medical advice about side effects. You may report side effects to FDA at 1-800-FDA-1088.

How should I store mometasone furoate cream, USP, 0.1%?• Store mometasone furoate cream, USP, 0.1% at 25°C (77°F); excursions permitted to 15-30°C (59-86°F) [see USP Controlled Room Temperature]. Avoid excessive heat.
• Keep mometasone furoate cream, USP, 0.1% and all medicines out of the reach of children.

General information about the safe and effective use of mometasone furoate cream, USP, 0.1%.Medicines are sometimes prescribed for purposes other than those listed in a Patient Information leaflet. Do not use mometasone furoate cream, USP, 0.1% for a condition for which it was not prescribed. Do not give mometasone furoate cream, USP, 0.1% to other people, even if they have the same symptoms that you have. It may harm them. You can ask your pharmacist or healthcare provider for information about mometasone furoate cream, USP, 0.1% that is written for health professionals.

What are the ingredients in mometasone furoate cream, USP, 0.1%?

Active ingredient:mometasone furoate
Inactive ingredients:hexylene glycol, phosphoric acid, propylene glycol stearate, stearyl alcohol and ceteareth-20, titanium dioxide, aluminum starch ocetnylsuccinate, white wax, white petrolatum, and purified water.

Distributed by:
Cosette Pharmaceuticals, Inc.
South Plainfield, NJ 07080

8-0634CPLNC2 Revised: 03/2022 VC7619

This Patient Information has been approved by the U.S. Food and Drug Administration.

Relabeled By: Preferred Pharmaceuticals Inc.

PRINCIPAL DISPLAY PANEL

NDC 68788-4075-4

Mometasone Furoate Cream, USP 0.1%

45 g

Rx only

FOR TOPICAL USE ONLY.

NOT FOR OPHTHALMIC USE.

Cosette Pharmaceuticals, Inc.

Relabeled By: Preferred Pharmaceuticals Inc.